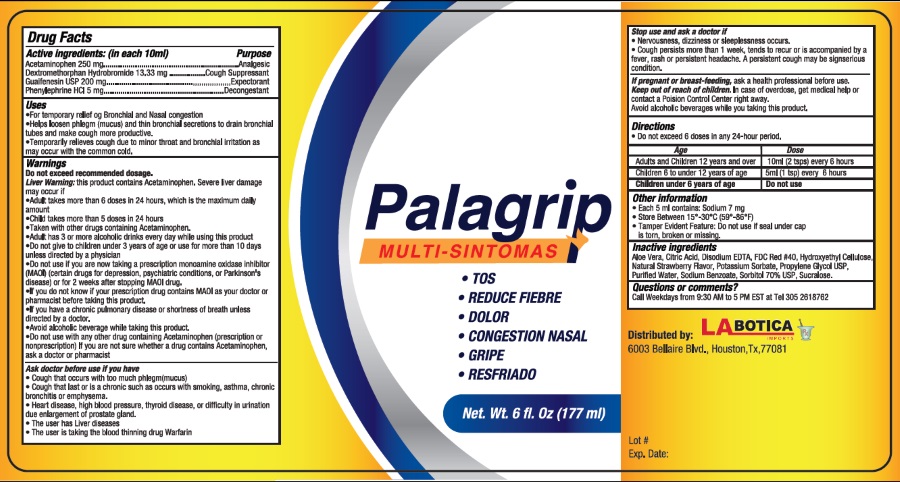 DRUG LABEL: Palagrip
NDC: 53149-2001 | Form: LIQUID
Manufacturer: All Pharma, LLC
Category: otc | Type: HUMAN OTC DRUG LABEL
Date: 20190614

ACTIVE INGREDIENTS: ACETAMINOPHEN 250 mg/10 mL; DEXTROMETHORPHAN HYDROBROMIDE 13.33 mg/10 mL; GUAIFENESIN 200 mg/10 mL; PHENYLEPHRINE HYDROCHLORIDE 5 mg/10 mL
INACTIVE INGREDIENTS: ALOE VERA WHOLE; ANHYDROUS CITRIC ACID; EDETATE DISODIUM; FD&C RED NO. 40; HYDROXYMETHYL CELLULOSE; WATER; SODIUM BENZOATE; SORBITOL; SUCRALOSE; PROPYLENE GLYCOL

ACTIVE INGREDIENT

Acvtive ingredients: (in 10 ml) Purpose

Acetaminophen 200 mg ............................. Analgesic

Dextromethorphan HBr 13.33 mg ................... Cough Suppressant

Guaifenesin 200 mg ................................... Expectorant

Phenylephrine HCl 5 mg ............................. Decongestant

Purpose

Analgesic

Cough Suppressant

Expectorant

Decongestant

Uses

- For temporary relief of bronchial and nasal congestion
- Help loosen phlegm (mucus) and thin bronchial secretions to drain bronchial tubes and make cough more productive.
- Teporarily relieves cough due to minor throat and bronchial irritation as may occur with the common cold

Warnings

Do not exceed recommended dosage

Liver warning: This product contains Acetaminophen. Sever liver damage may occur if

- Adult takes more than 6 doses in 24 hours, which is the maximum daily amount
- Child takes more than 5 doses in 24 hours
- Taken with other drugs containing Acetaminophen
- Adult has 3 or more alcoholic drinks everyday while using this product
- Do not give to children under 3 years of age or use for more than 10 days unless directed by a physician

Do not use

- If you are now taking a prescription monoamine oxidase inhibitor (MAOI)(certain drugs for depression , psychiatric conditions, or Parkinson’s disease) or for 2 weeks after stopping the MAOI drug.
- if you do not know if your prescription drug contains on MAOI ask your doctor or pharmacist before taking this product
- if you have a chronic pulmonary disease or shortness of breath unless directed by a doctor
- avoid alcoholic beverages while you are taking this product
- do not use with any other drug containing Acetaminophen (prescirption or nonprescription). If you are not sure whether a drug contains Acetaminophen, ask a doctor or a pharmacist.

Ask the doctor before use if you have

- cough that occurs with too much phlegm (mucus)
- cough that lasts or is chronic such as occurs with smoking, asthma, chronic bronchitis or emphysema
- heart disease, high blood pressure, thyroid disease, or difficulty in urination due to the enlargement of prostate gland.
- The user has liver disease
- The user is taking the blood thinning drug Warfarin.

Stop use and ask the doctor if

- Nervoisness, dizziness or sleeplessness occurs.
- Cough persists for more than 1 week, tends to recur, or accompanied by fever, rash or persistent headache. A persistent cough may be sign of a serious condition

PREGNANCY OR BREAST FEEDING

If pregnant or breast-feeding, ask a health professional before use.

Keep out of reach of children. In case of overdose, get medical help or contact a Poison Control Center right away.

Directions

- Do not take more than 6 doses in any 24-hour period

Age Dose

Adults and children 12 years and over 10 mL (2 tsps) every 6 hours

Children 6 to under 12 years of age. 5 mL (1 tsps) every 6 hours

Children under 6 years of age Do not use

Inactive ingredients

Aloe vera, citric acid, disodium EDTA, FD&C Red #40, hydroxyethyl cellulose, natural strawberry flavor, propylene glycol, water, sodium benzoate, sorbitol 70%, sucralose